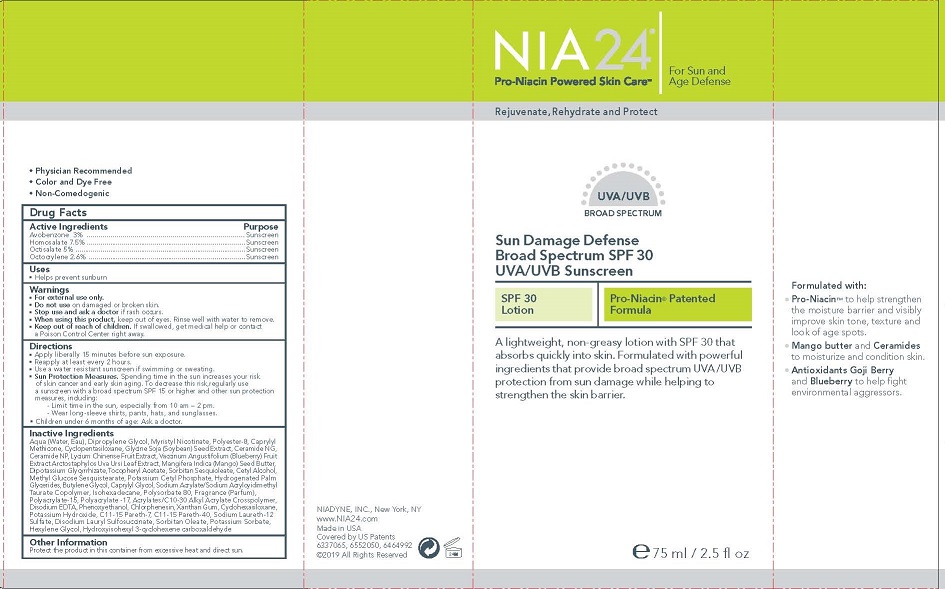 DRUG LABEL: NIA24 SUN DAMAGE DEFENSE BROAD SPECTRUM UVA/UVB SUNSCREEN
NDC: 43115-102 | Form: LOTION
Manufacturer: NIADYNE INC
Category: otc | Type: HUMAN OTC DRUG LABEL
Date: 20201231

ACTIVE INGREDIENTS: AVOBENZONE 3 g/100 mL; HOMOSALATE 7.5 g/100 mL; OCTISALATE 5 g/100 mL; OCTOCRYLENE 2.6 g/100 mL
INACTIVE INGREDIENTS: WATER; DIPROPYLENE GLYCOL; MYRISTYL NICOTINATE; POLYESTER-8 (1400 MW, CYANODIPHENYLPROPENOYL CAPPED); CAPRYLYL TRISILOXANE; CYCLOMETHICONE 5; SOYBEAN; CERAMIDE NG; CERAMIDE NP; LYCIUM CHINENSE FRUIT; BLUEBERRY; ARCTOSTAPHYLOS UVA-URSI LEAF; MANGIFERA INDICA SEED BUTTER; GLYCYRRHIZINATE DIPOTASSIUM; .ALPHA.-TOCOPHEROL; SORBITAN SESQUIOLEATE; CETYL ALCOHOL; METHYL GLUCOSE SESQUISTEARATE; POTASSIUM CETYL PHOSPHATE; HYDROGENATED PALM GLYCERIDES; BUTYLENE GLYCOL; CAPRYLYL GLYCOL; SODIUM ACRYLATE/SODIUM ACRYLOYLDIMETHYLTAURATE COPOLYMER (4000000 MW); ISOHEXADECANE; POLYSORBATE 80; AMMONIUM ACRYLOYL DIMETHYLTAURATE/METHACRYLATE, DIMETHYLACRYLAMIDE AND METHACRYLIC ACID COPOLYMER, PPG-3 GLYCERYL TRIACRYLATE CROSSLINKED (100000 MW); CARBOMER COPOLYMER TYPE A (ALLYL PENTAERYTHRITOL CROSSLINKED); EDETATE DISODIUM; PHENOXYETHANOL; CHLORPHENESIN; XANTHAN GUM; CYCLOMETHICONE 6; POTASSIUM HYDROXIDE; C11-15 PARETH-7; C11-15 PARETH-40; SODIUM LAURETH-12 SULFATE; DISODIUM LAURYL SULFOSUCCINATE; SORBITAN MONOOLEATE; POTASSIUM SORBATE; HEXYLENE GLYCOL; HYDROXYISOHEXYL 3-CYCLOHEXENE CARBOXALDEHYDE

NIA24 SUN DAMAGE DEFENSE BROAD SPECTRUM SPF 30 UVA/UVB SUNSCREEN

Active Ingredients

Avobenzone 3%
Homosalate 7.5%
Octisalate 5%
Octocrylene 2.6%

Purpose

Sunscreen

Warnings

- For external use only.
- Do not use on damaged or broken skin.
- Stop use and ask a doctor if rash occurs.
- When using this product, keep out of eyes. Rinse well with water to remove.

Keep out of reach of children. If swallowed, get medical help or contact a Poison Control Center right away.

Directions

- Apply liberally 15 minutes before sun exposure.
- Reapply at least every 2 hours.
- Use a water-resistant sunscreen if swimming or sweating.
- Sun Protection Measures. Spending time in the sun increases your risk of skin cancer and early skin aging. To decrease this risk, regularly use a sunscreen witha broad spectrum SPF 15 or higher and other sun protection measures, including:
  - Limit time in the sun, especially from 10 am – 2 pm.
  - Wear long-sleeve shirts, pants, hats, and sunglasses.
- Children under 6 months of age: Ask a doctor.

Other information

Protect the product in this container from excessive heat and direct sun.

Inactive Ingredients

Aqua (Water, Eau), Dipropylene Glycol, Myristyl Nicotinate, Polyester-8, Caprylyl Methicone, Cyclopentasiloxane, Glycine Soja (Soybean) Seed Extract, Ceramide NG, Ceramide NP, Lycium Chinense Fruit Extract, Vaccinum Angustifolium (Blueberry) Fruit Extract Arctostaphylos Uva Ursi Leaf Extract, Mangifera Indica (Mango) Seed Butter, Dipotassium Glycyrrhizate, Tocopheryl Acetate, Sorbitan Sesquioleate, Cetyl Alcohol, Methyl Glucose Sesquistearate, Potassium Cetyl Phosphate, Hydrogenated Palm Glycerides, Butylene Glycol, Caprylyl Glycol, Sodium Acrylate/Sodium Acryloyidimethyl Taurate Copolymer, Isohexadecane, Polysorbate 80, Fragrance (Parfum),
Polyacrylate-15, Polyacrylate -17, Acrylates/C10-30 Alkyl Acrylate Crosspolymer, Disodium EDTA, Phenoxyethanol, Chlorphenesin, Xanthan Gum, Cyclohexasiloxane, Potassium Hydroxide, C11-15 Pareth-7, C11-15 Pareth-40, Sodium Laureth-12 Sulfate, Disodium Lauryl Sulfosuccinate, Sorbitan Oleate, Potassium Sorbate, Hexylene Glycol, Hydroxyisohexyl 3-cyclohexene carboxaldehyde